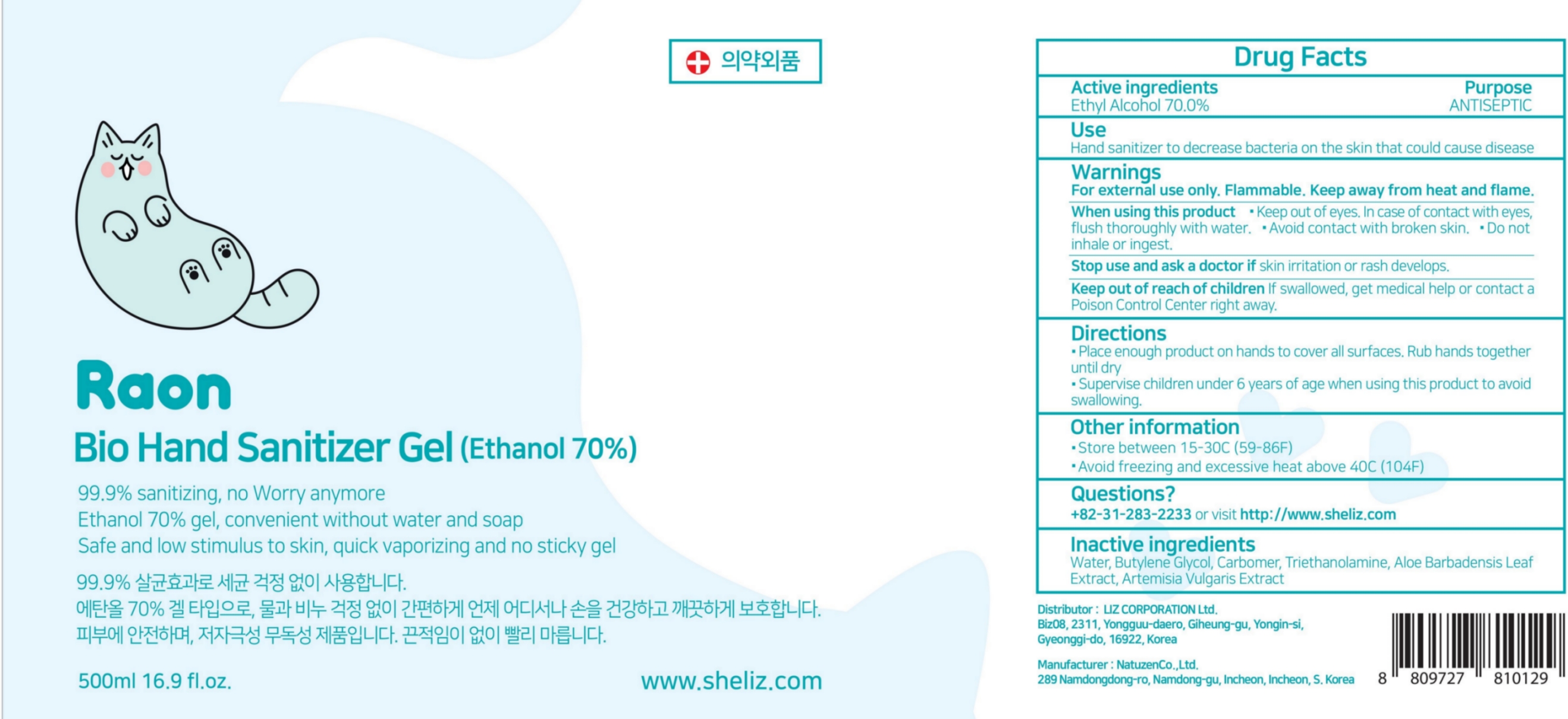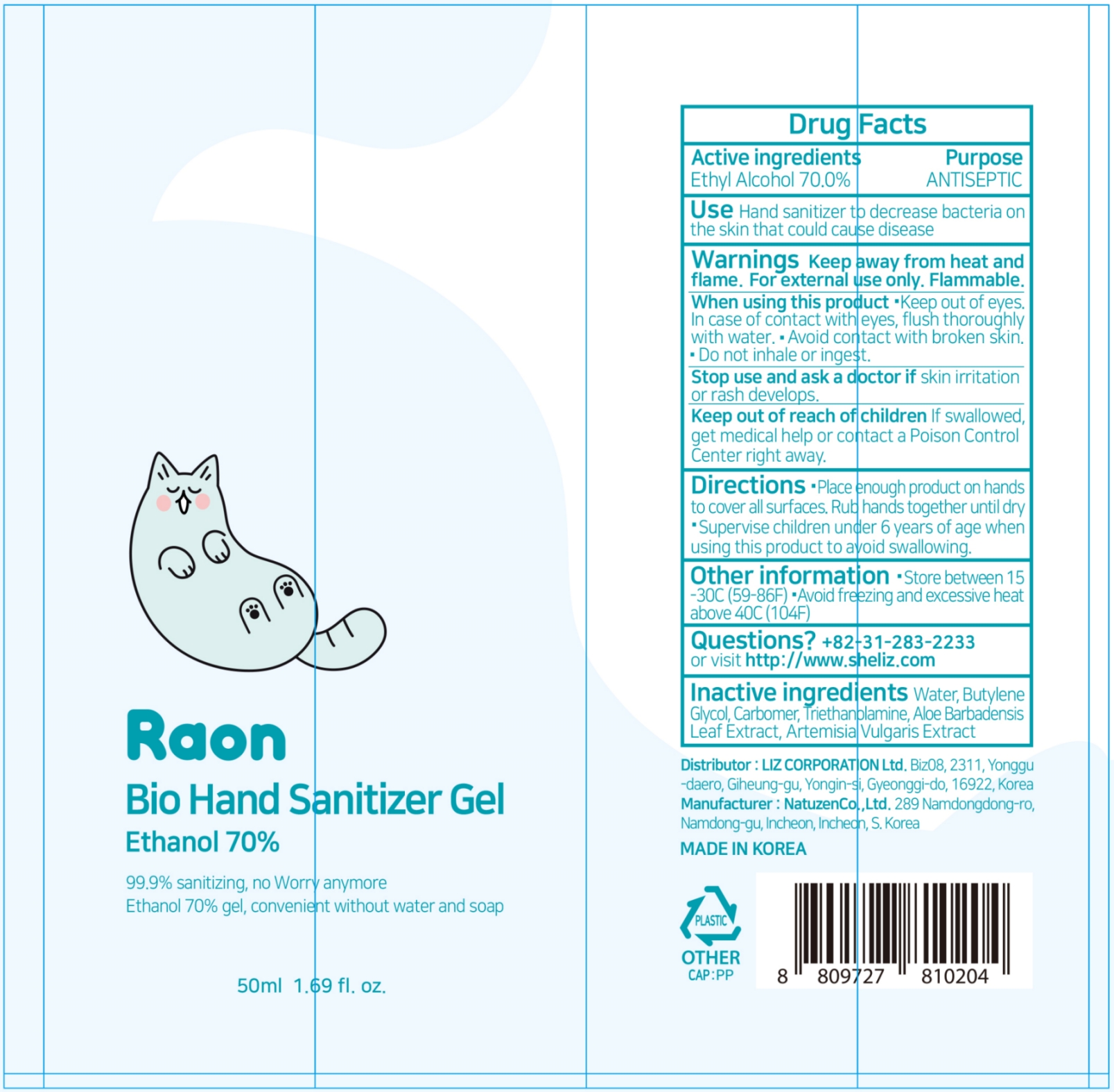 DRUG LABEL: Raon Hand Sanitizer Gel
NDC: 79487-202 | Form: GEL
Manufacturer: Liz Corporation Co., Ltd
Category: otc | Type: HUMAN OTC DRUG LABEL
Date: 20210222

ACTIVE INGREDIENTS: ALCOHOL 70 mg/100 mL
INACTIVE INGREDIENTS: WATER; ALOE VERA LEAF; CARBOMER HOMOPOLYMER, UNSPECIFIED TYPE; TROLAMINE; BUTYLENE GLYCOL; ARTEMISIA VULGARIS ROOT

79487-202 Raon Hand Sanitizer Gel

Active ingredients

Ethyl Alcohol 70.0%

Purpose

ANTISEPTIC

Use

Hand sanitizer to decrease bacteria on the skin that could cause disease

Warnings

For external use only. Flammable. Keep away from heat and flame.

When using this product

Keep out of eyes. In case of contact with eyes, flush thoroughly with water. Avoid contact with broken skin. Do not inhale or ingest.

Stop use and ask a doctor if

skin irritation or rash develops.

Keep out of reach of children

If swallowed, get medical help or contact a Poison Control Center right away.

Directions

Place enough product on hands to cover all surfaces. Rub hands together until dry

Superevise children under 6 years of age when using this product to avoid swalloing.

Other information

Store between 15-30ºC (59-86ºF)

Avoid Freezing and excessive heat above 40ºC (104ºF)

Inactive ingredients

Water, Butylene Glycol, Carbomer, Triethanplamine, Aloe Barbadensis Leaf Extract, Artemisia Vulgaris Extract